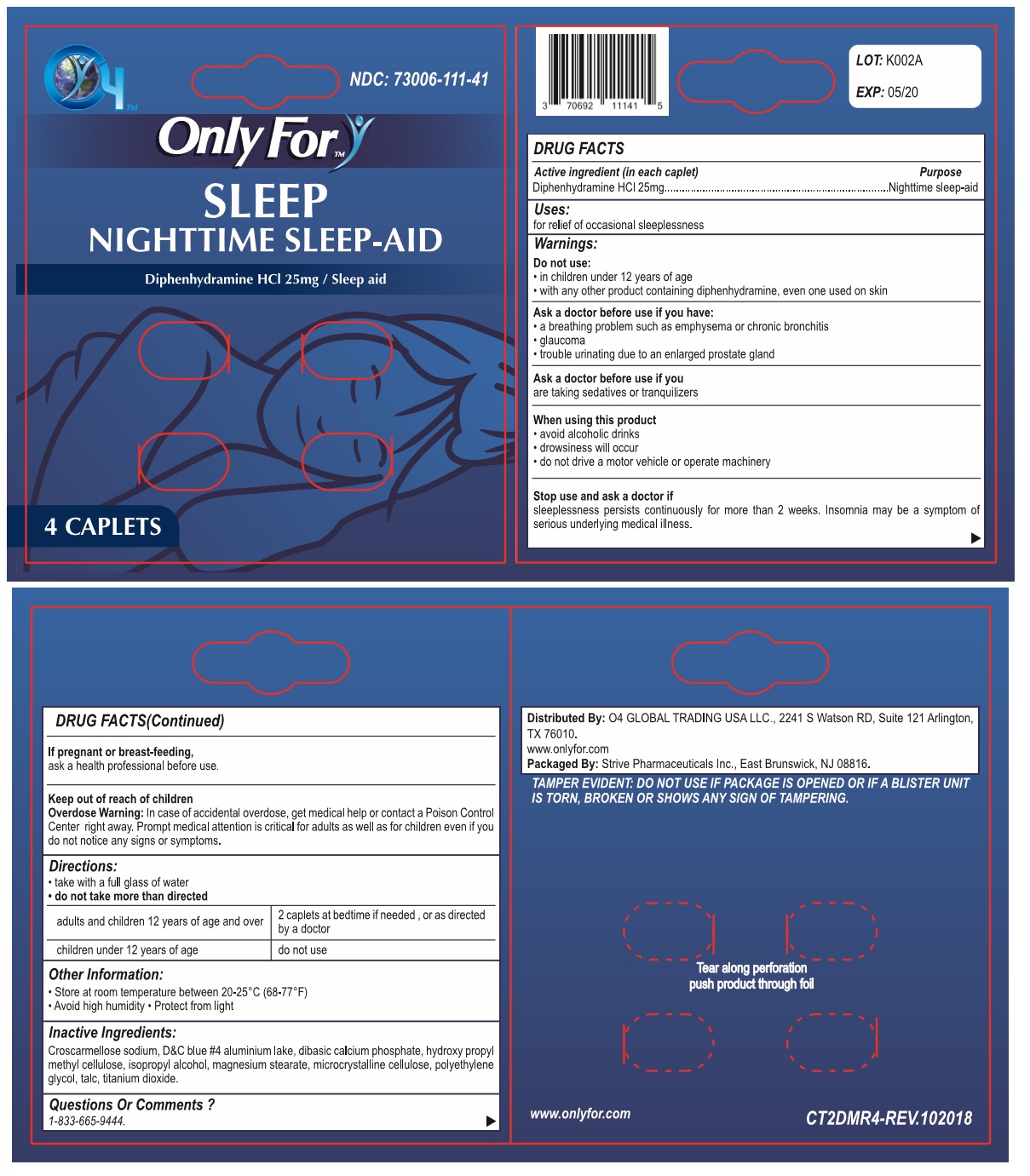 DRUG LABEL: Only For
NDC: 73006-111 | Form: TABLET
Manufacturer: O4 Global Trading Usa, Llc 
Category: otc | Type: HUMAN OTC DRUG LABEL
Date: 20190425

ACTIVE INGREDIENTS: DIPHENHYDRAMINE HYDROCHLORIDE 25 mg/1 1
INACTIVE INGREDIENTS: CROSCARMELLOSE SODIUM; D&C BLUE NO. 4; DIBASIC CALCIUM PHOSPHATE DIHYDRATE; HYPROMELLOSE 2910 (5 MPA.S); ISOPROPYL ALCOHOL; MAGNESIUM PALMITOSTEARATE; MICROCRYSTALLINE CELLULOSE 101; POLYETHYLENE GLYCOL 400; TALC; TITANIUM DIOXIDE

Only For- SLEEP

Active ingredient (in each caplet)

Diphenhydramine HCL 25mg

Purpose

Nighttime sleep-aid

Uses:

for relief of occasional sleeplessness

Warnings:

Do not use:

- in children under 12 years of age
- with any other product containing diphenhydramine, even one used on skin

Ask a doctor before use if you have:

- a breathing problem such as emphysema or chronic bronchitis
- glaucoma
- trouble urinating due to an enlarged prostate gland

Ask a doctor before use if you
are taking sedatives or tranquilizers

When using this product

- avoid alcoholic drinks
- drowsiness will occur
- do not drive a motor vehicle or operate machinery

Stop use and ask a doctor if
sleeplessness persists continuously for more than 2 weeks. Insomnia may be a symptom of serious underlying medical illness.

If pregnant or breast-feeding,
ask a health professional before use.

Keep out of reach of children

Overdose Warning: In case of accidental overdose, get medical help or contact a Poison Control Center right away. Prompt medical attention is critical for adults as well as for children even if you do not notice any signs or symptoms.

Directions:

- take with a full glass of water
- do not take more than directed
  adults and children 12 years of age and over | 2 caplets at bedtime if needed, or as directed by a doctor
  children under 12 years of age | do not use

Other Information:

- Store at room temperature between 20-25°C (68-77°F)
- Avoid high humidity • Protect from light

Inactive Ingredients:

Croscarmellose sodium, D&C blue #4 aluminium lake, dibasic calcium phosphate, hydroxy propyl methyl cellulose, isopropyl alcohol, magnesium stearate, microcrystalline cellulose, polyethylene glycol, talc, titanium dioxide.

Questions Or Comments ?

1-833-665-9444.

NDC: 73006-111-41

NIGHTTIME SLEEP-AID

Distributed By: O4 GLOBAL TRADING USA LLC., 2241 S Watson RD, Suite 121 Arlington, TX 76010.

www.onlyfor.com

Packaged By: Strive Pharmaceuticals Inc., East Brunswick, NJ 08816.

TAMPER EVIDENT: DO NOT USE IF PACKAGE IS OPENED OR IF A BLISTER UNIT IS TORN, BROKEN OR SHOWS ANY SIGN OF TAMPERING.

Tear along perforation push product through foil